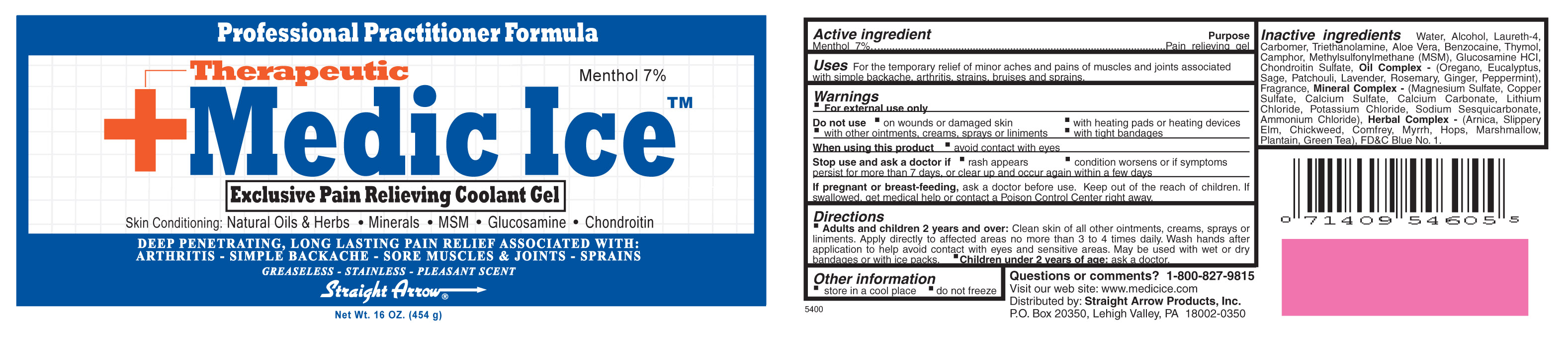 DRUG LABEL: Medic Ice
								
NDC: 62001-0318 | Form: GEL
Manufacturer: Straight Arrow Products, Inc.
Category: otc | Type: HUMAN OTC DRUG LABEL
Date: 20100927

ACTIVE INGREDIENTS: MENTHOL .07 g/1 g
INACTIVE INGREDIENTS: WATER; ALCOHOL; TROLAMINE; CARBOMER INTERPOLYMER TYPE A (55000 CPS); BENZOCAINE; LAURETH-4; THYMOL; ENGLISH LAVENDER OIL; ALOE; DIMETHYL SULFONE; CAMPHOR (SYNTHETIC); PEPPERMINT OIL; EUCALYPTUS OIL; MAGNESIUM SULFATE, UNSPECIFIED; ROSEMARY OIL; PATCHOULI OIL; GINGER OIL; SAGE OIL; OREGANO; GLUCOSAMINE; CHONDROITIN SULFATE (BOVINE); LITHIUM CHLORIDE; POTASSIUM CHLORIDE; CUPRIC SULFATE ANHYDROUS; AMMONIUM CHLORIDE; CALCIUM SULFATE; CALCIUM CARBONATE; ARNICA MONTANA; ELM; STELLARIA MEDIA; COMFREY; MYRRH; HOPS; PLANTAGO MAJOR; GREEN TEA LEAF; ALTHAEA OFFICINALIS ROOT; FD&C BLUE NO. 1

Active Ingredient
Menthol 7%

Purpose
Pain relieving gel

Keep out of reach of children. If swallowed, get medical help or contact a Poison Control Center right away.

Uses
For the temporary relief of minor aches and pains of muscles and joints associated with simple backache, arthritis, strains, bruises and sprains.

WARNINGS

- For external use only

Do not use

- on wounds or damaged skin
- with heating pads or heating devices
- with other ointments, creams, sprays or liniments
- with tight bandages

When using this product

- avoid contact with eyes

Stop use and ask a doctor if:

- a rash appears
- condition worsens or if symptoms persist for more than 7 days, or clear up and occur again within a few days

PREGNANCY OR BREAST FEEDING

If pregnant or breast-feeding, ask a doctor before use.

Directions

- Adults and children 2 years and over: Clean skin of all other ointments, creams, sprays or liniments. Apply directly to affected areas no more than 3 to 4 times daily. Wash hands after application to help avoid contact with eyes and sensitive areas. May be used with wet or dry bandages or with ice packs.
- Children under 2 years of age: ask a doctor

INACTIVE INGREDIENT

Inactive Ingredients Water, Alcohol, Laureth-4, Carbomer, Triethanolamine, Aloe Vera, Benzocaine, Thymol, Camphor, Methylsulfonylmethane (MSM), Glucosamine HCl, Chondroitin Sulfate, Oil Complex - (Oregano, Eucalyptus, Sage, Patchouli, Lavender, Rosemary, Ginger, Peppermint), Fragrance, Mineral Complex - (Magnesium Sulfate, Copper Sulfate, Calcium Sulfate, Calcium Carbonate, Lithium Chloride, Potassium Chloride, Sodium Sesquicarbonate, Ammonium Chloride), Herbal Complex - (Arnica, Slippery Elm, Chickweed, Comfrey, Myrrh, Hops, Marshmallow, Plantain, Green Tea), FD and C Blue No. 1.

PACKAGE LABEL

ID: Med1
Descriptive Text: Medic Ice label
File Name: medicice.jpg